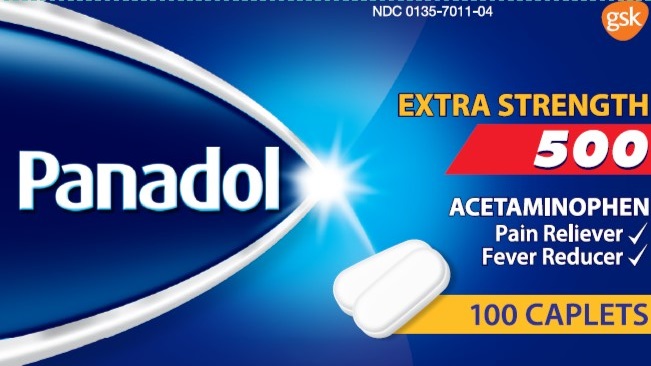 DRUG LABEL: PANADOL

NDC: 0135-7011 | Form: TABLET, FILM COATED
Manufacturer: Haleon US Holdings LLC
Category: otc | Type: HUMAN OTC DRUG LABEL
Date: 20240206

ACTIVE INGREDIENTS: ACETAMINOPHEN 500 mg/1 1
INACTIVE INGREDIENTS: CASTOR OIL; HYPROMELLOSE, UNSPECIFIED; POVIDONE, UNSPECIFIED; STARCH, CORN; SODIUM STARCH GLYCOLATE TYPE A CORN; STEARIC ACID

Drug Facts

Active ingredient (in each caplet)

Acetaminophen 500 mg

Purpose

Pain reliever/Fever reducer

Uses

- temporarily relieves minor aches and pains due to:
  - headache
  - muscular aches
  - backache
  - minor arthritis pain
- temporarily reduces fever

Warnings

Liver warning:This product contains acetaminophen. Severe liver damage may occur if you take

- more than 8 caplets in 24 hours, which is the maximum daily amount
- with other drugs containing acetaminophen
- 3 or more alcoholic drinks every day while using this product

Allergy alert:Acetaminophen may cause severe skin reactions. Symptoms may include:

- skin reddening
- blisters
- rash

If a skin reaction occurs, stop use and seek medical help right away.

Do not use

- with any other drug containing acetaminophen (prescription or nonprescription). If you are not sure whether a drug contains acetaminophen, ask a doctor or pharmacist.
- if you are allergic to acetaminophen or any of the inactive ingredients in this product

Ask a doctor before use if you have

liver disease

Ask a doctor or pharmacist before use if you are

taking the blood thinning drug warfarin

Stop use and ask a doctor if

- pain gets worse or lasts more than 10 days
- fever gets worse or lasts more than 3 days
- redness or swelling is present
- any new symptoms appear

These could be signs of a serious condition.

If pregnant or breast-feeding,

ask a health professional before use.

Overdose warning:

Taking more than the recommended dose can cause serious health problems. In case of overdose, get medical help or contact a Poison Control Center right away. Quick medical attention is critical for adults as well as for children even if you do not notice any signs or symptoms.

Directions

- do not take more than directed(see overdose warning)
- adults and children 12 years of age and over: take 2 caplets every 6 hours, while symptoms persist or as directed by a doctor
- do not take more than 8 caplets in 24 hours, unless directed by a doctor
- children under 12 years of age: ask a doctor

Other information

- store at 25°C (77°F)
- close cap tightly after use

Inactive ingredients

castor oil, hypromellose, povidone, pregelatinized starch, sodium starch glycolate, stearic acid

Questions?

1-800-455-7139

Principal Display Panel

NDC 0135-7011-04

PANADOL

EXTRA STRENGTH

500

ACETAMINOPHEN

Pain Reliever

Fever Reducer

100 CAPLETS

Distributed by:

GSK Consumer Healthcare

Warren, NJ 07059

©2020 GSK group of companies or its licensor.

Trademarks are owned by or licensed to the GSK group of companies.

Tamper-Evident Feature:Do not use if printed inner safety seal under cap is broken or missing.

READ AND KEEP CARTON FOR COMPLETE INFORMATION

B-0630-764-12 Front Carton